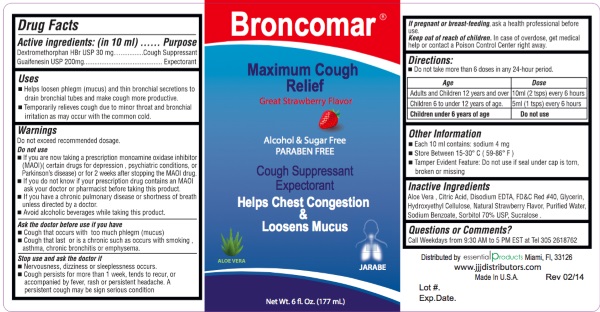 DRUG LABEL: Broncomar
NDC: 70242-103 | Form: LIQUID
Manufacturer: Dannso Corp./d.b.a. Essential Products
Category: otc | Type: HUMAN OTC DRUG LABEL
Date: 20160101

ACTIVE INGREDIENTS: DEXTROMETHORPHAN HYDROBROMIDE 30 mg/10 mL; GUAIFENESIN 200 mg/10 mL
INACTIVE INGREDIENTS: ALOE VERA LEAF; CITRIC ACID MONOHYDRATE; EDETATE DISODIUM; FD&C RED NO. 40; HYDROXYETHYL CELLULOSE (100 MPA.S AT 2%); WATER; SODIUM BENZOATE; SUCRALOSE

Broncomar Maximum Cought Relief

Active Ingredients:(in each 10 ml.) | Purpose
Dextromethorphan Hydrobromide 30 mg .................... | Cough Suppressant
Guaifenesin 200 mg....................................................... | Expectorant

Uses:

- Helps loosen phlegm (mucus) and thin bronchial secretions to drain bronchial tubes and make cough more productive.
- Temporarily relieves cough due to minor throat and bronchial irritation as may occur with the common cold.

Warnings

Do not exceed recommended dosage

Do not use

- If you are now taking a prescription monoamine oxidase inhibitor (MAOI) (certain drugs for depression, psychiatric conditions, or Parkinson's disease) or for 2 weeks after stopping MAOI drug.
- If you do not know if your prescription drug contains MAOI as your doctor or pharmacist before taking this product.
- If you have a chronic pulmonary disease or shortness of breath unless directed by a doctor.
- Avoid alcoholic beverage while taking this product.

Stop use and ask a doctor

- Nervousness, dizziness or sleeplessness occurs.
- Cough persists more than 1 week, tends to recur or is accompanied by a fever, rash or persistent headache. A persistent cough may be signserious condition.

Ask doctor before use if you have

- Cough that occurs with too much phlegm(mucus)
- Cough that last or is a chronic such as occurs with smoking, asthma, chronic bronchitis or emphysema.

PREGNANCY OR BREAST FEEDING

If pregnant or breast-feeding ask a health professional before use.

Keep out of reach of children.

In case of overdose, get medical help or contact a Poison Control Center right away.

Directions

- Do not exceed 6 doses in any 24 hour period.

AGE | DOSE
Adults and Children 12 years and over | 10 ml (2 tsps) every 6 hours
Children 6 to under 12 years of age | 5 ml (1 tsp) every 6 hours
Children under 6 years of age | Do not use

Other Information:

- Each 10 mls contains: sodium 4 mg
- Store between 15 - 30 degrees Celsius (59 - 86 Fahrenheit).
- Tamper Evident Feature:Do not use if seal under cap is torn, broken or missing.

Inactive Ingredient

Aloe Vera, Citric Acid, Disodium EDTA, FDC Red #40, Glycerin, Hydroxyethyl Cellulose, Natural Strawberry Flavor, Purified Water, Sodium Benzoate, Sorbitol 70% USP, Sucralose.

Questions or Comments

Call Weekdays from 9:30 AM to 5PM EST at Tel 305-261-762

Distributed by

Essential Products Miami FL 33126

www.jjjdistributors.com

Made in U.S.A.